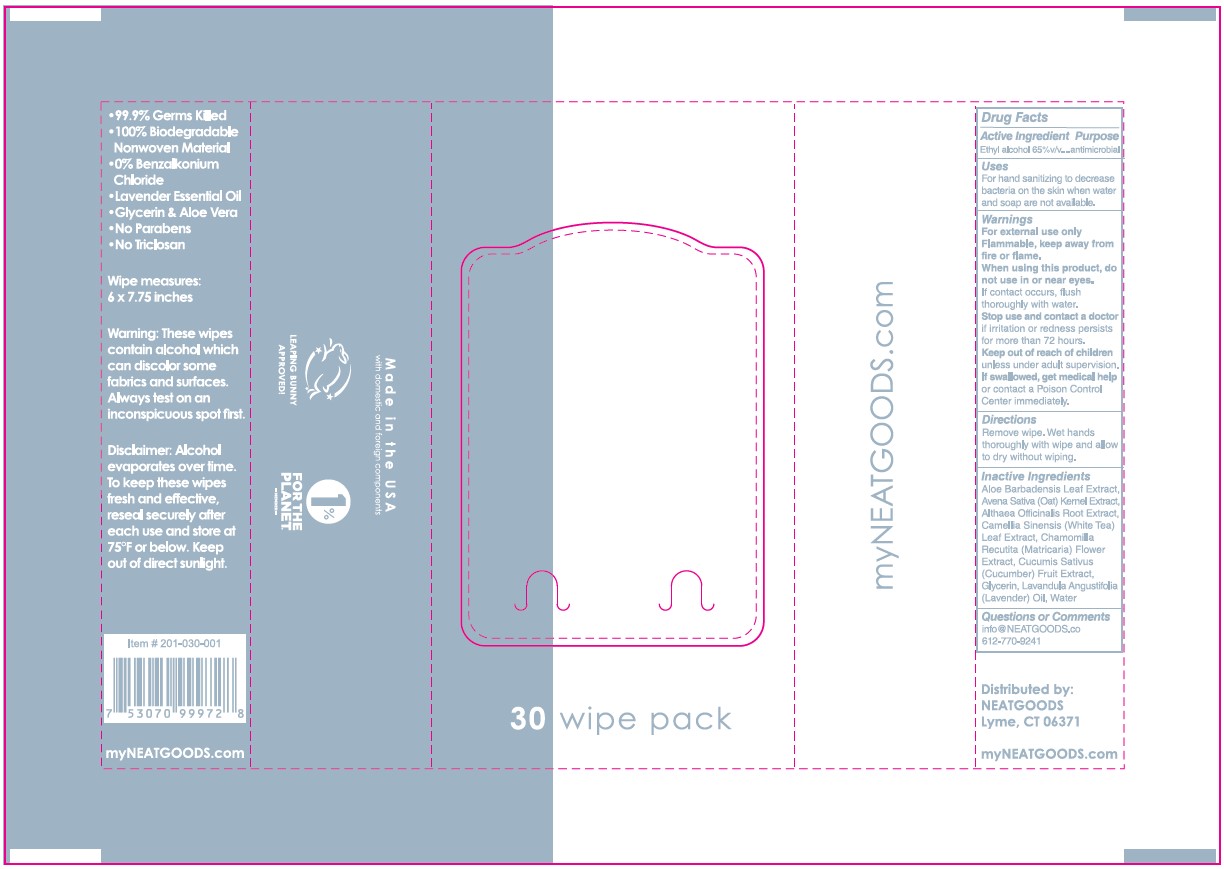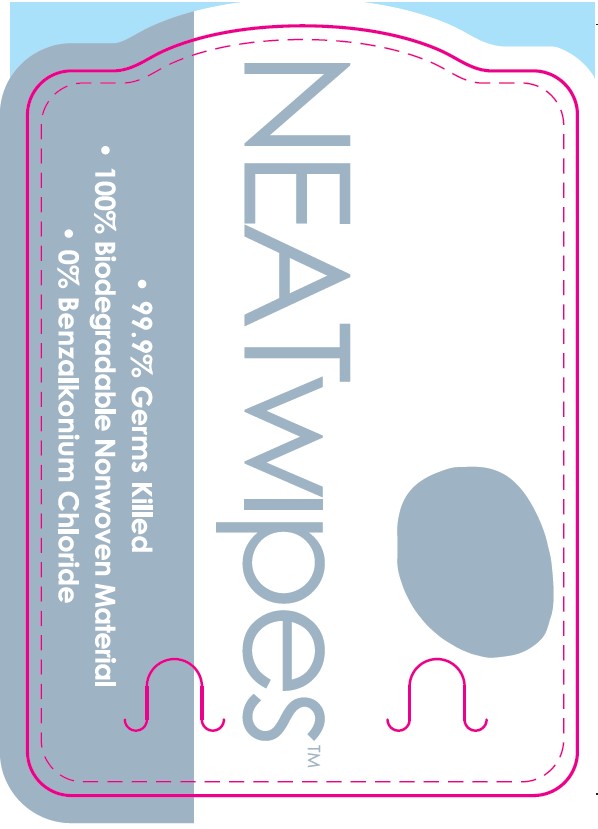 DRUG LABEL: Hand Sanitizing Wipe
NDC: 81339-200 | Form: CLOTH
Manufacturer: NeatGoods LLC
Category: otc | Type: HUMAN OTC DRUG LABEL
Date: 20220510

ACTIVE INGREDIENTS: ALCOHOL 65 mL/100 mL
INACTIVE INGREDIENTS: ALTHAEA OFFICINALIS ROOT; WATER; OAT; LAVENDER OIL; GREEN TEA LEAF; CUCUMBER; GLYCERIN; CHAMOMILE; ALOE VERA LEAF

NEATwipes

Active Ingredient

Ethyl Alcohol – 65% v/v

Purpose

Antimicrobial

Uses

For hand sanitizing to decrease bacteria on the skin when water and soap are not available.

Warnings

For external use only

Flammable, keep away from fire or flame.

When using this product, do not use in or near eyes.

If contact occurs, flush thoroughly with water.

Stop use and contact a doctor if irritation or redness persists for more than 72 hours.

Keep out of reach of children unless under adult supervision.

If swallowed, get medical help or contact a Poison Control Center immediately.

Directions

Remove wipe.

Wet hands thoroughly with wipe and allow to dry without wiping.

Inactive Ingredients

Aloe Barbadensis Leaf Extract, Avena Sativa (Oat) Kernel Extract, Althaea Officinalis Root Extract, Camellia Sinensis (White Tea) Leaf Extract, Chamomilla Recutita (Matricaria) Flower Extract, Cucumis Sativus (Cucumber) Fruit Extract, Glycerin, Lavandula Angustifolia (Lavender) Oil, Water

Questions or Comments

info@NEATGOODS.co or 612-770-9241

Label

NEATwipesTM

• 99.9% Germs Killed

• 100% Biodegradable Nonwoven Material

• 0% Benzalkonium Chloride

30 wipe pack

• Lavender Essential Oil

• Glycerin & Aloe Vera

• No Parabens

• No Triclosan

Wipe measures: 6 x 7.75 inches

Warning: These wipes contain alcohol which can discolor same fabrics

and surfaces. Always test an inconspicuous spot first.

Disclaimer: Alcohol evaporates over time. To keep these wipes fresh

and effective, reseal securely sfter each use and store at 75ºF or below.

Keep out of direct sunlight.

Item #: 201-030-001

7 53070 99972 8

my NEATGOODS.COM

Made in USA

with domestic and foreign components

LEAPING BUNNY APPROVED!

1% FOR THE PLANET. -MEMBER-

Distributed by:

NEATGOODS Lyme, CT 06371

from domestic and imported ingredients